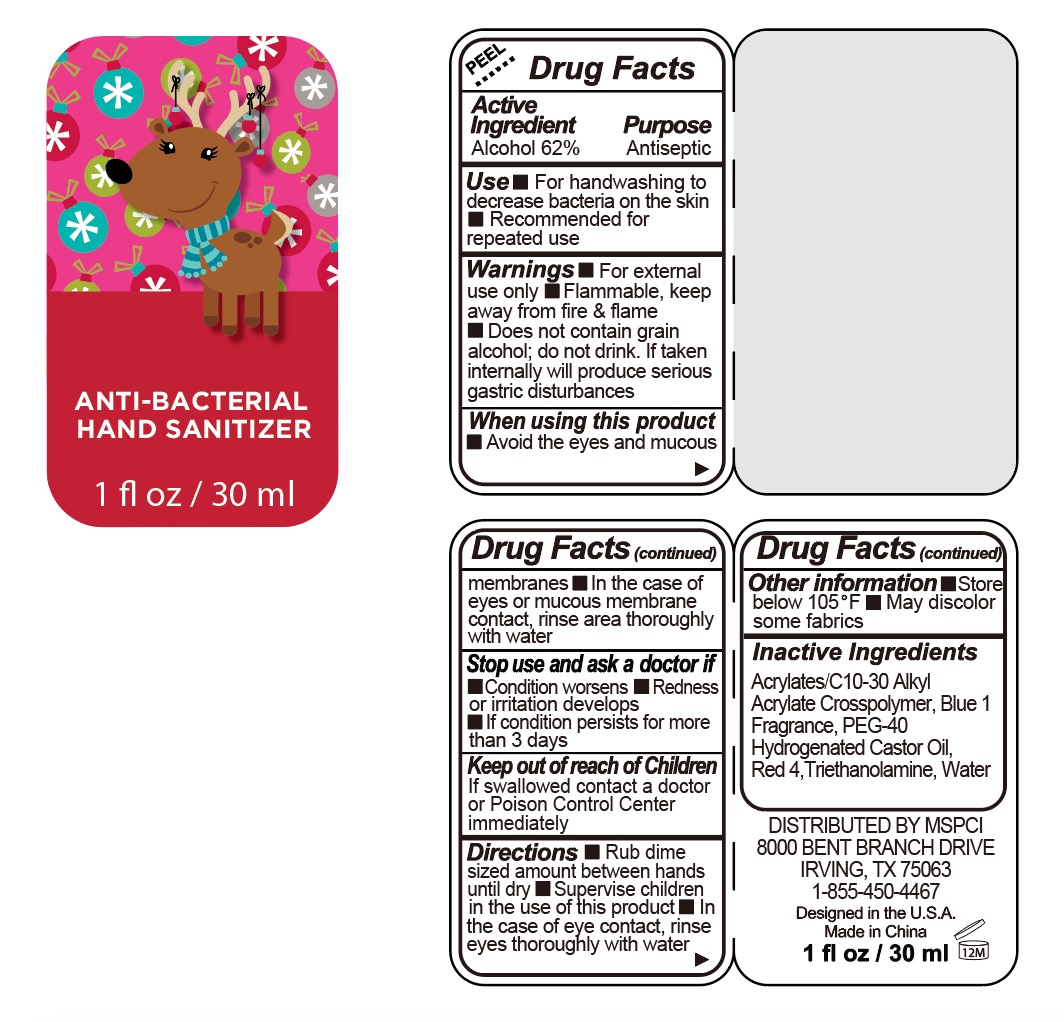 DRUG LABEL: ANTI BACTERIAL
NDC: 60675-009 | Form: LIQUID
Manufacturer: Michaels Stores Procurement Company
Category: otc | Type: HUMAN OTC DRUG LABEL
Date: 20160726

ACTIVE INGREDIENTS: ALCOHOL 62 g/100 mL
INACTIVE INGREDIENTS: POLYOXYL 40 HYDROGENATED CASTOR OIL; CARBOMER INTERPOLYMER TYPE A (55000 CPS); WATER; TROLAMINE; FD&C BLUE NO. 1; FD&C RED NO. 4

Drug Facts

Active Ingredient

Alcohol 62%

Purpose

Antiseptic

Use

■ For handwashing to decrease bacteria on the skin

■ Recommended for repeated use

Warnings

■ For external use only ■ Flammable, keep away from fire & flame ■ Does not contain grain alcohol;do not drink. If taken internally will produce serious gastric disturbances

When using this product

■ Avoid the eyes and mucous membranes ■ In the case of eyes or mucous membrane contact, rinse area thoroughly with water

Stop use and ask a doctor if

■ Condition worsens ■ Redness or irritation develops ■ If condition persists for more than 3 days

Keep out of reach of children

If swallowed contact a doctor or Poison Control Center immediately.

Directions

■ Rub dime sized amount between hands until dry ■ Supervise children in the use of this product ■ In the case of eye contact, rinse eyes thoroughly with water

Other information

■ Store below 105°F ■ May discolor some fabrics

Inactive Ingredients

Acrylates/C10-30 Alkyl Acrylate Crosspolymer, Blue 1, Fragrance, PEG-40 Hydrogenated Castor Oil, Red 4, Triethanolamine, Water